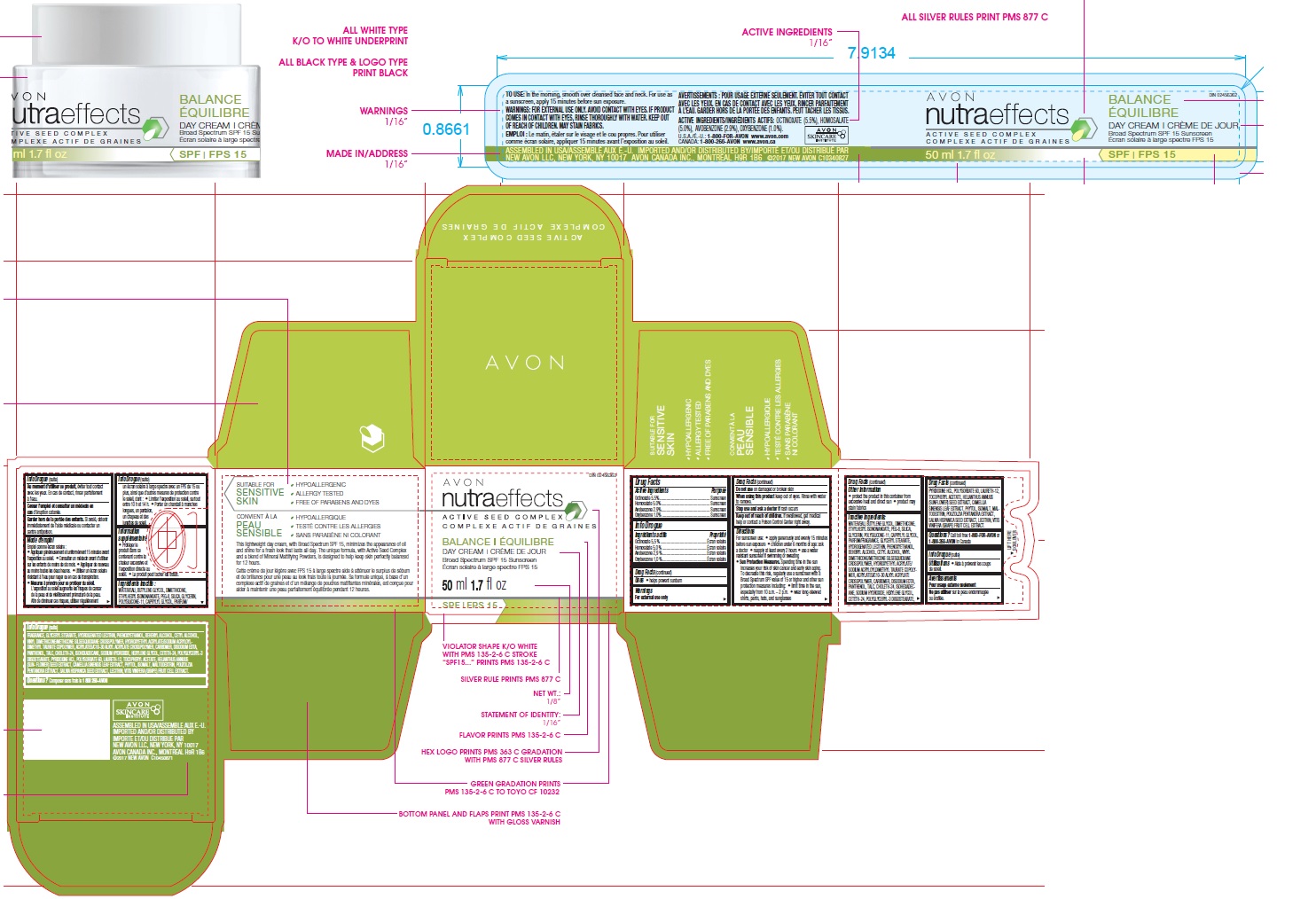 DRUG LABEL: Nutra Effects Balance Day Cream SPF15
NDC: 10096-9502 | Form: CREAM
Manufacturer: New Avon LLC
Category: otc | Type: HUMAN OTC DRUG LABEL
Date: 20180402

ACTIVE INGREDIENTS: OCTINOXATE 5.5 g/100 g; OXYBENZONE 1 g/100 g; HOMOSALATE 5 g/100 g; AVOBENZONE 2.9 g/100 g
INACTIVE INGREDIENTS: WATER

Nutra Effects Balance Day Cream SPF15

ACTIVE INGREDIENT

Active Ingredients/Ingrédients actifs:

OCTINOXATE (5.5 %), HOMOSALATE (5.0 %), AVOBENZONE (2.9 %), OXYBENZONE (1.0 %).

INDICATIONS & USAGE

Uses

- helps prevent sunburn

WARNINGS

For external use only

Do not use on damaged or broken skin

When using this product keep out of eyes. Rinse with water to remove.

Stop use and ask a doctor if rash occurs

Keep out of reach of children. If swallowed, get medical help or contact a Poison Control Center right away.

DOSAGE & ADMINISTRATION

Directions

- For sunscreen use:
- apply generously and evenly 15 minutes before sun exposure
- children under 6 months of age: ask a doctor
- reapply at least every 2 hours
- use a water resistant sunscreen if swimming or sweating

Sun Protection Measures. Spending time in the sun increases your risk of skin cancer and early skin aging. To decrease this risk, regularly use a sunscreen with a Broad Spectrum SPF value of 15 or higher and other sun protection measures including:

- limit time in the sun, especially from 10 a.m. – 2 p.m.
- wear long-sleeved shirts, pants, hats, and sunglasses

Other Information

- protect the product in this container from excessive heat and direct sun
- product may stain fabrics

INACTIVE INGREDIENT

Inactive Ingredients/Ingrédients inactifs: WATER/EAU, BUTYLENE GLYCOL, DIMETHICONE, ETHYLHEXYL ISONONANOATE, PEG-8, SILICA, GLYCERIN, POLYSILICONE-11, CAPRYLYL GLYCOL, PARFUM/FRAGRANCE, GLYCERYL STEARATE, HYDROGENATED LECITHIN, PHENOXYETHANOL, BEHENYL ALCOHOL, CETYL ALCOHOL, VINYL DIMETHICONE/METHICONE SILSESQUIOXANE CROSSPOLYMER, HYDROXYETHYL ACRYLATE/SODIUM ACRYLOYLDIMETHYL TAURATE COPOLYMER, ACRYLATES/C10-30 ALKYL ACRYLATE CROSSPOLYMER, CARBOMER, DISODIUM EDTA, PANTHENOL, TALC, CHOLETH-24, ISOHEXADECANE, SODIUM HYDROXIDE, HEXYLENE GLYCOL, CETETH-24, POLYGLYCERYL-3 DIISOSTEARATE, PYRIDOXINE HCL, POLYSORBATE 60, LAURETH-12, TOCOPHERYL ACETATE, HELIANTHUS ANNUUS (SUNFLOWER) SEED EXTRACT, CAMELLIA SINENSIS LEAF EXTRACT, PHYTOL, ISOMALT, MALTODEXTRIN, POUZOLZIA PENTANDRA EXTRACT, SALVIA HISPANICA SEED EXTRACT, LECITHIN, VITIS VINIFERA (GRAPE) FRUIT CELL EXTRACT.

QUESTIONS

Questions or Comments?
Call toll free 1-800-FOR-AVON or 1-800-265-AVON in Canada